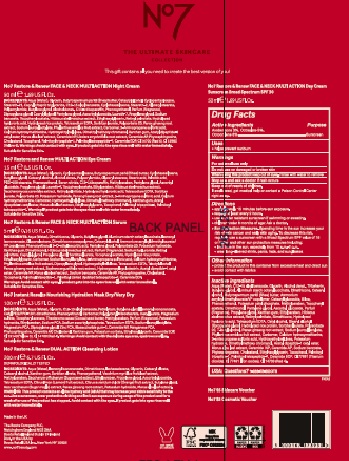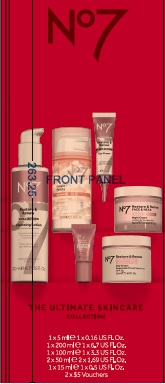 DRUG LABEL: No7Restore and Renew Face and Neck Multi Action Day Cream Sunscreen Broad Spectrum SPF 30
NDC: 11489-195 | Form: CREAM
Manufacturer: BCM Ltd
Category: otc | Type: HUMAN OTC DRUG LABEL
Date: 20230814

ACTIVE INGREDIENTS: AVOBENZONE 1.5 g/1 g; OCTISALATE 2.5 g/1 g; OCTOCRYLENE 4.0 g/1 g
INACTIVE INGREDIENTS: WATER; ALKYL (C12-15) BENZOATE; GLYCERIN; alcohol; TRIBEHENIN; BUTYLENE GLYCOL; ALUMINUM STARCH OCTENYLSUCCINATE; DIMETHICONE; CETOSTEARYL ALCOHOL; SHEA BUTTER; AMMONIUM ACRYLOYLDIMETHYLTAURATE/VP COPOLYMER; CETEARYL GLUCOSIDE; SILICON DIOXIDE; PHENOXYETHANOL; POTASSIUM CETYL PHOSPHATE; METHYLPARABEN; .ALPHA.-TOCOPHEROL ACETATE; DIMETHICONOL (100000 CST); PENTYLENE GLYCOL; ASCORBYL GLUCOSIDE; PROPYLENE GLYCOL; XANTHAN GUM; ETHYLPARABEN; ABELMOSCHUS MANIHOT WHOLE; VITAMIN A PALMITATE; HYALURONIC ACID; EDETATE SODIUM TETRAHYDRATE; CETYL ALCOHOL; STEARYL ALCOHOL; DIPROPYLENE GLYCOL; RICE BRAN; SORBITAN MONOLAURATE; POLYSORBATE 20; TERT-BUTYL ALCOHOL; PANAX GINSENG ROOT OIL; SODIUM LAUROYL LACTYLATE; PHYLLANTHUS EMBLICA FRUIT; CARBOMER 940; DESMENINOL CALCIUM; HYDROXYETHYL CELLULOSE (100 MPA.S AT 2%); POTASSIUM HYDROXIDE; DIMETHYLMETHOXY CHROMANOL; N-ACETYL DIPEPTIDE-1; MORUS ALBA LEAF; CERAMIDE 3; CERAMIDE 6 II; SODIUM BENZOATE; PHYTOSPHINGOSINE; CHOLESTEROL; ETHYLHEXYLGLYCERIN; TOCOPHEROL; CERAMIDE 9; TITANIUM DIOXIDE; BROWN IRON OXIDE; PALMITOYL TRIPEPTIDE-1; PALMITOYL TETRAPEPTIDE-7; FD&C RED NO. 4

No7 Restore and Renew Face and Neck Multi Action Day Cream Sunscreen Broad Spectrum SPF 30

Carton Active Ingredients Section

Active ingredients

Avobenzone 3%

Octisalate 5%

Octocrylene 8%

Uses

Uses - helps prevent sunburn

Warnings

For external use only

Do not use on damaged or broken skin

When using this product keep out of eyes. Rinse with water to remove.

Ask a doctor

Stop use and ask a doctor if rash occurs

Keep out of reach of children

If swallowed, get medical help or contact a Poison Control Center right away

Directions

Apply liberally 15 minutes before sun exposure

reapply at least every 2 hours

use a water resistant sunscreen if swimming or sweating

children under 6 months of age: Ask a doctor

Sun Protection Measures. Spending time in the sun increases your risk of skin cancer and early skin aging.

To decrease this risk, regularly use a sunscreen with a Broad Spectrum SPF value of 15 or higher and other sun protection measures including:

Limit time in the sun, especially from 10 a.m - 2 p.m.

wear long-sleeved shirts,pants,hats and sunglasses.

Storage

Other information

Protect the product in this container from excessive heat and direct sun

Avoid contact with fabrics

Inactive ingredients

Aqua(Water), C12-15 alkyl benzoate, Glycerin, Alcohol denat, Tribehenin, Butylene Glycol, Auminum starch octenylsuccinate, Dimethicone, Cetearyl glycol, Butyrospermum parkii(Shea)butter, Ammonium acryloydimethyltaurate/VP copolymer, Cetearyl glucoside, Silica, Phenoxyethanol, Potassium cetyl phosphate, Methylparaben, Tocopheryl acetate, Dimethiconol, Pentylene glycol, Ascorbyl glucoside, Parfum (Fragrance), Propylene glycol, Xanthan gum, TEthylparaben, Hibiscus abelmoschus extract, Retinyl palmitate, Simethicone, Hydrolyzed hyaluronic acid, Testrasodium EDTA, Cetyl alcohol, Stearyl alcohol, Dipropylene glycol, Hydrolyzed rice protein, Sorbitan laurate, Polysorbate 20, T-butyl alcohol, Panax ginseng root extract, Sodium lauroyl lactylate, Phyllanthus emblica fruit extract, Carbomer, Calcium hydroxymethionine, 3-aminopropane sulfonic acid, Hydroxyethylcellulose, Potassium hydroxide, Dimethylmethoxy chromanol, Morus alba leaf extract, Ceramide NP, Ceramide AP, Sodium benzoate, Phytosphingsine, Cholesterol, Ethylhexylglycerin, Tocopherol, Palmitoyl tripeptide-1, Palmitoyl tetrapeptide-7, Ceramide EOP, CI 77891 (Titanium dioxide), CI 77491 (Iron oxides) CI 14700(Red 4)

Cartonone

The Boots Company PLC Nottingham England NG2 3AA
Boots Retail Ireland Dublin 24 Ireland
Dist. in the USA by Boots Retail USA Inc. New York NY 10005
www.no7beauty.com

Made in the UK

cartonone

cartontwo